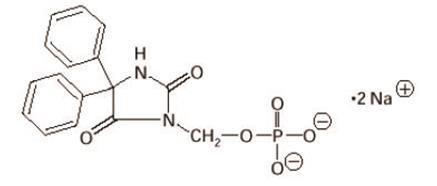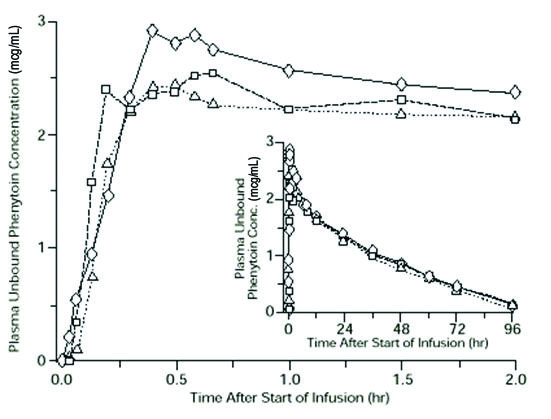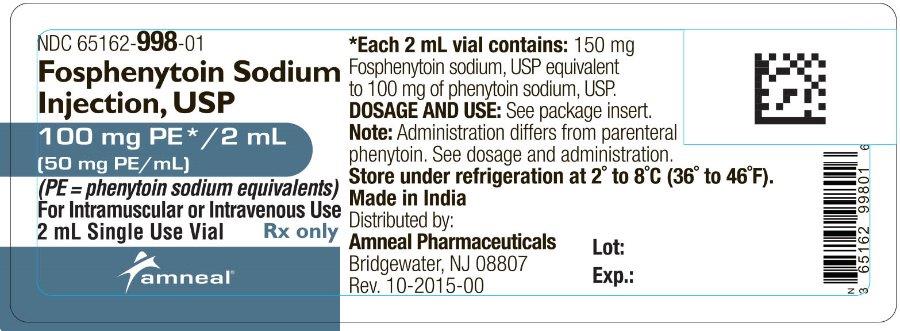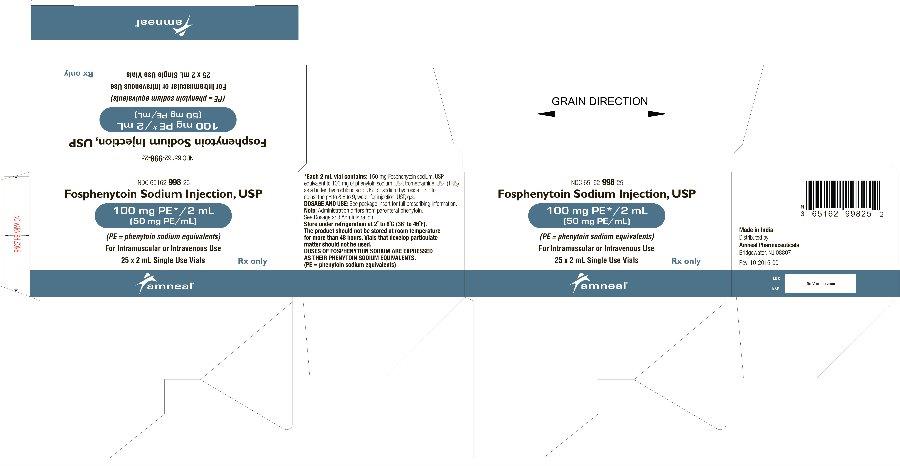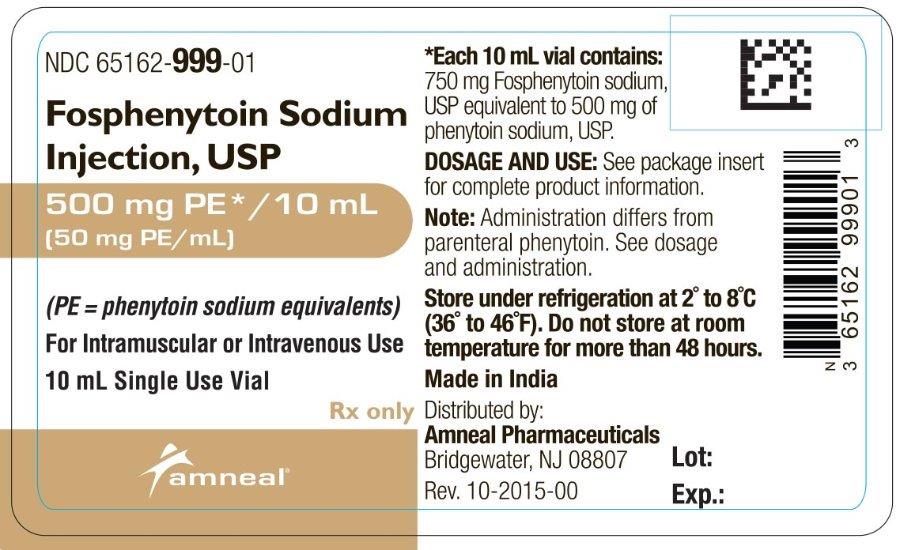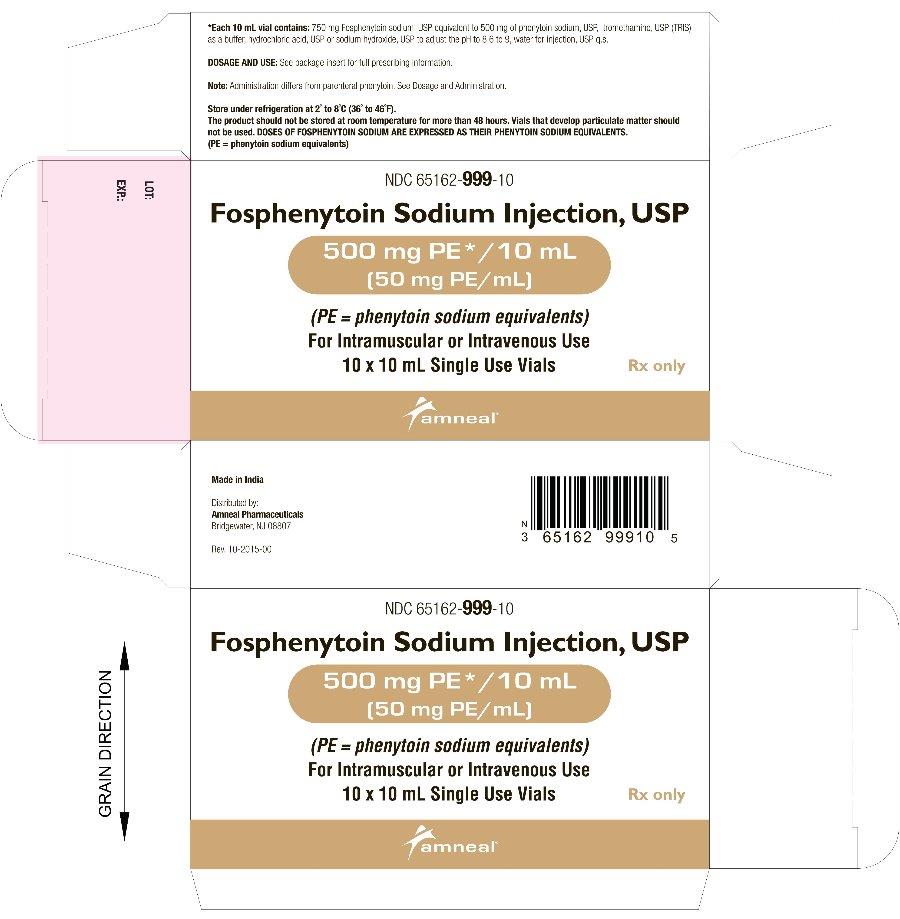 DRUG LABEL: Fosphenytoin Sodium
NDC: 65162-998 | Form: INJECTION
Manufacturer: Amneal Pharmaceuticals LLC
Category: prescription | Type: HUMAN PRESCRIPTION DRUG LABEL
Date: 20241025

ACTIVE INGREDIENTS: FOSPHENYTOIN SODIUM 50 mg/1 mL
INACTIVE INGREDIENTS: WATER; TROMETHAMINE; HYDROCHLORIC ACID; SODIUM HYDROXIDE

Fosphenytoin Sodium Injection, USP
Rx Only

WARNING: CARDIOVASCULAR RISK ASSOCIATED WITH RAPID INFUSION RATES

The rate of intravenous fosphenytoin administration should not exceed 150 mg phenytoin sodium equivalents (PE) per minute because of the risk of severe hypotension and cardiac arrhythmias. Careful cardiac monitoring is needed during and after administering intravenous fosphenytoin. Although the risk of cardiovascular toxicity increases with infusion rates above the recommended infusion rate, these events have also been reported at or below the recommended infusion rate. Reduction in rate of administration or discontinuation of dosing may be needed (see WARNINGS and DOSAGE AND ADMINISTRATION).

DESCRIPTION

Fosphenytoin sodium injection, USP is a prodrug intended for parenteral administration; its active metabolite is phenytoin. 1.5 mg fosphenytoin sodium, USP (hereafter referred to as fosphenytoin) equivalent to 1 mg phenytoin sodium and is referred to as 1 mg phenytoin equivalents (PE). The amount and concentration of fosphenytoin is always expressed in terms of mg PE.

Fosphenytoin injection is marketed in 2 mL vials containing a total of 100 mg PE and 10 mL vials containing a total of 500 mg PE. The concentration of each vial is 50 mg PE/mL. Fosphenytoin is supplied in vials as a ready-mixed solution in Water for Injection, USP, and Tromethamine, USP (TRIS), buffer adjusted to pH 8.6 to 9.0 with either Hydrochloric Acid, NF, or Sodium Hydroxide, NF. Fosphenytoin injection is a clear, colorless to pale yellow, sterile solution.

The chemical name of fosphenytoin is 5,5-diphenyl-3-[(phosphonooxy)methyl]-2,4-imidazolidinedione disodium salt.

The molecular structure of fosphenytoin is:

The molecular weight of fosphenytoin is 406.24.

IMPORTANT NOTE: Throughout all fosphenytoin injection product labeling, the amount and concentration of fosphenytoin are always expressed in terms of phenytoin sodium equivalents (PE). Fosphenytoin’s weight is expressed as phenytoin sodium equivalents to avoid the need to perform molecular weight-based adjustments when substituting fosphenytoin for phenytoin or vice versa.

Care should be taken to ensure that fosphenytoin is always prescribed and dispensed in phenytoin sodium equivalents (PE) (see DOSAGE AND ADMINISTRATION).

CLINICAL PHARMACOLOGY

Introduction

Following parenteral administration of fosphenytoin injection, fosphenytoin is converted to the anticonvulsant phenytoin. For every mmol of fosphenytoin administered, one mmol of phenytoin is produced. The pharmacological and toxicological effects of fosphenytoin include those of phenytoin. However, the hydrolysis of fosphenytoin to phenytoin yields two metabolites, phosphate and formaldehyde. Formaldehyde is subsequently converted to formate, which is in turn metabolized via a folate dependent mechanism. Although phosphate and formaldehyde (formate) have potentially important biological effects, these effects typically occur at concentrations considerably in excess of those obtained when fosphenytoin is administered under conditions of use recommended in this labeling.

Mechanism of Action

Fosphenytoin is a prodrug of phenytoin and accordingly, its anticonvulsant effects are attributable to phenytoin.

After IV administration to mice, fosphenytoin blocked the tonic phase of maximal electroshock seizures at doses equivalent to those effective for phenytoin. In addition to its ability to suppress maximal electroshock seizures in mice and rats, phenytoin exhibits anticonvulsant activity against kindled seizures in rats, audiogenic seizures in mice, and seizures produced by electrical stimulation of the brainstem in rats. The cellular mechanisms of phenytoin thought to be responsible for its anticonvulsant actions include modulation of voltage-dependent sodium channels of neurons, inhibition of calcium flux across neuronal membranes, modulation of voltage-dependent calcium channels of neurons, and enhancement of the sodium-potassium ATPase activity of neurons and glial cells. The modulation of sodium channels may be a primary anticonvulsant mechanism because this property is shared with several other anticonvulsants in addition to phenytoin.

Pharmacokinetics and Drug Metabolism

Fosphenytoin

Absorption/Bioavailability:

Intravenous: When fosphenytoin is administered by IV infusion, maximum plasma fosphenytoin concentrations are achieved at the end of the infusion. Fosphenytoin has a half-life of approximately 15 minutes.

Intramuscular: Fosphenytoin is completely bioavailable following IM administration of fosphenytoin. Peak concentrations occur at approximately 30 minutes postdose. Plasma fosphenytoin concentrations following IM administration are lower but more sustained than those following IV administration due to the time required for absorption of fosphenytoin from the injection site.

Distribution: Fosphenytoin is extensively bound (95% to 99%) to human plasma proteins, primarily albumin. Binding to plasma proteins is saturable with the result that the percent bound decreases as total fosphenytoin concentrations increase. Fosphenytoin displaces phenytoin from protein binding sites. The volume of distribution of fosphenytoin increases with fosphenytoin dose and rate, and ranges from 4.3 to 10.8 liters.

Metabolism and Elimination: The conversion half-life of fosphenytoin to phenytoin is approximately 15 minutes. The mechanism of fosphenytoin conversion has not been determined, but phosphatases probably play a major role. Fosphenytoin is not excreted in urine. Each mmol of fosphenytoin is metabolized to 1 mmol of phenytoin, phosphate, and formate (see CLINICAL PHARMACOLOGY, Introduction and PRECAUTIONS, Phosphate Load for Renally Impaired Patients).

Phenytoin (after fosphenytoin administration)

In general, IM administration of fosphenytoin generates systemic phenytoin concentrations that are similar enough to oral phenytoin sodium to allow essentially interchangeable use.

The pharmacokinetics of fosphenytoin following IV administration of fosphenytoin, however, are complex, and when used in an emergency setting (e.g., status epilepticus), differences in rate of availability of phenytoin could be critical. Studies have therefore empirically determined an infusion rate for fosphenytoin that gives a rate and extent of phenytoin systemic availability similar to that of a 50 mg/min phenytoin sodium infusion.

A dose of 15 to 20 mg PE/kg of fosphenytoin infused at 100 to 150 mg PE/min yields plasma free phenytoin concentrations over time that approximate those achieved when an equivalent dose of phenytoin sodium (e.g., parenteral phenytoin sodium) is administered at 50 mg/min (see DOSAGE AND ADMINISTRATION and WARNINGS).

FIGURE 1. Mean plasma unbound phenytoin concentrations following IV administration of 1200 mg PE fosphenytoin infused at 100 mg PE/min (triangles) or 150 mg PE/min (squares) and 1200 mg phenytoin sodium infused at 50 mg/min (diamonds) to healthy subjects (N = 12). Inset shows time course for the entire 96-hour sampling period.

Following administration of single IV fosphenytoin doses of 400 to 1200 mg PE, mean maximum total phenytoin concentrations increase in proportion to dose, but do not change appreciably with changes in infusion rate. In contrast, mean maximum unbound phenytoin concentrations increase with both dose and rate.

Absorption/Bioavailability: Fosphenytoin is completely converted to phenytoin following IV administration, with a half-life of approximately 15 minutes. Fosphenytoin is also completely converted to phenytoin following IM administration and plasma total phenytoin concentrations peak in approximately 3 hours.

Distribution: Phenytoin is highly bound to plasma proteins, primarily albumin, although to a lesser extent than fosphenytoin. In the absence of fosphenytoin, approximately 12% of total plasma phenytoin is unbound over the clinically relevant concentration range. However, fosphenytoin displaces phenytoin from plasma protein binding sites. This increases the fraction of phenytoin unbound (up to 30% unbound) during the period required for conversion of fosphenytoin to phenytoin (approximately 0.5 to 1 hour post infusion).

Metabolism and Elimination: Phenytoin derived from administration of fosphenytoin is extensively metabolized in the liver and excreted in urine primarily as 5-(p-hydroxyphenyl)-5-phenylhydantoin and its glucuronide; little unchanged phenytoin (1% to 5% of the fosphenytoin dose) is recovered in urine. Phenytoin is metabolized by the cytochrome P450 enzymes CYP2C9 and CYP2C19. Phenytoin hepatic metabolism is saturable, and following administration of single IV fosphenytoin doses of 400 to 1200 mg PE, total and unbound phenytoin AUC values increase disproportionately with dose. Mean total phenytoin half-life values (12 to 28.9 hr) following fosphenytoin injection administration at these doses are similar to those after equal doses of parenteral phenytoin sodium and tend to be greater at higher plasma phenytoin concentrations.

Special Populations

Patients with Renal or Hepatic Disease: Due to an increased fraction of unbound phenytoin in patients with renal or hepatic disease, or in those with hypoalbuminemia, the interpretation of total phenytoin plasma concentrations should be made with caution (see DOSAGE AND ADMINISTRATION). Unbound phenytoin concentrations may be more useful in these patient populations. After IV administration of fosphenytoin to patients with renal and/or hepatic disease, or in those with hypoalbuminemia, fosphenytoin clearance to phenytoin may be increased without a similar increase in phenytoin clearance. This has the potential to increase the frequency and severity of adverse events (see PRECAUTIONS).

Age: The effect of age was evaluated in patients 5 to 98 years of age. Patient age had no significant impact on fosphenytoin pharmacokinetics. Phenytoin clearance tends to decrease with increasing age (20% less in patients over 70 years of age relative to that in patients 20 to 30 years of age). Phenytoin dosing requirements are highly variable and must be individualized (see DOSAGE AND ADMINISTRATION).

Gender and Race: Gender and race have no significant impact on fosphenytoin or phenytoin pharmacokinetics.

Pediatrics: The safety and efficacy of fosphenytoin in pediatric patients have not been established.

Clinical Studies

Infusion tolerance was evaluated in clinical studies. One double-blind study assessed infusion-site tolerance of equivalent loading doses (15 to 20 mg PE/kg) of fosphenytoin infused at 150 mg PE/min or phenytoin infused at 50 mg/min. The study demonstrated better local tolerance (pain and burning at the infusion site), fewer disruptions of the infusion, and a shorter infusion period for fosphenytoin-treated patients (Table 1).

TABLE 1. Infusion Tolerance of Equivalent Loading Doses of IV Fosphenytoin and IV Phenytoin
 | IV Fosphenytoin N=90 | IV Phenytoin N=22
Local Intolerance | 9%a | 90%
Infusion Disrupted | 21% | 67%
Average Infusion Time | 13 min | 44 min
a Percent of patients

Fosphenytoin-treated patients, however, experienced more systemic sensory disturbances (see PRECAUTIONS, Sensory Disturbances).

Infusion disruptions in fosphenytoin-treated patients were primarily due to systemic burning, pruritus, and/or paresthesia while those in phenytoin-treated patients were primarily due to pain and burning at the infusion site (see Table 1).

In a double-blind study investigating temporary substitution of fosphenytoin for oral phenytoin, IM fosphenytoin was as well-tolerated as IM placebo. IM fosphenytoin resulted in a slight increase in transient, mild to moderate local itching (23% of patients vs 11% of IM placebo-treated patients at any time during the study). This study also demonstrated that equimolar doses of IM fosphenytoin may be substituted for oral phenytoin sodium with no dosage adjustments needed when initiating IM or returning to oral therapy. In contrast, switching between IM and oral phenytoin requires dosage adjustments because of slow and erratic phenytoin absorption from muscle.

INDICATIONS AND USAGE

Fosphenytoin sodium injection, USP is indicated for the control of generalized tonic-clonic status epilepticus and prevention and treatment of seizures occurring during neurosurgery. Fosphenytoin can also be substituted, short-term, for oral phenytoin. Fosphenytoin should be used only when oral phenytoin administration is not possible. Fosphenytoin must not be given orally.

CONTRAINDICATIONS

Fosphenytoin sodium injection, USP is contraindicated in patients who have demonstrated hypersensitivity to fosphenytoin sodium injection, USP or its ingredients, or to phenytoin or other hydantoins.

Because of the effect of parenteral phenytoin on ventricular automaticity, fosphenytoin injection is contraindicated in patients with sinus bradycardia, sino-atrial block, second and third degree A-V block, and Adams-Stokes syndrome.

Coadministration of fosphenytoin is contraindicated with delavirdine due to potential for loss of virologic response and possible resistance to delavirdine or to the class of non-nucleoside reverse transcriptase inhibitors.

WARNINGS

DOSES OF FOSPHENYTOIN ARE ALWAYS EXPRESSED IN TERMS OF MILLIGRAMS OF PHENYTOIN SODIUM EQUIVALENTS (mg PE). 1 mg PE IS EQUIVALENT TO 1 mg PHENYTOIN SODIUM.

DO NOT, THEREFORE, MAKE ANY ADJUSTMENT IN THE RECOMMENDED DOSES WHEN SUBSTITUTING FOSPHENYTOIN FOR PHENYTOIN SODIUM OR VICE VERSA. FOR EXAMPLE, IF A PATIENT IS RECEIVING 1000 mg PE OF FOSPHENYTOIN, THAT IS EQUIVALENT TO 1000 mg OF PHENYTOIN SODIUM.

The following warnings are based on experience with fosphenytoin or phenytoin.

Dosing Errors

Do not confuse the amount of drug to be given in PE with the concentration of the drug in the vial.

Medication errors associated with fosphenytoin have resulted in patients receiving the wrong dose of fosphenytoin. Fosphenytoin is marketed in 2 mL vials containing a total of 100 mg PE and 10 mL vials containing a total of 500 mg PE. The concentration of each vial is 50 mg PE/mL. Errors have occurred when the concentration of the vial (50 mg PE/mL) was misinterpreted to mean that the total content of the vial was 50 mg PE. These errors have resulted in two- or ten-fold overdoses of fosphenytoin since each vial actually contains a total of 100 mg PE or 500 mg PE. In some cases, ten-fold overdoses were associated with fatal outcomes. To help minimize confusion, the prescribed dose of fosphenytoin should always be expressed in milligrams of phenytoin equivalents (mg PE) (see DOSAGE AND ADMINISTRATION). Additionally, when ordering and storing fosphenytoin, consider displaying the total drug content (i.e., 100 mg PE/2 mL or 500 mg PE/10 mL) instead of concentration in computer systems, pre-printed orders, and automated dispensing cabinet databases to help ensure that total drug content can be clearly identified. Care should be taken to ensure the appropriate volume of fosphenytoin is withdrawn from the vial when preparing the drug for administration. Attention to these details may prevent some fosphenytoin medication errors from occurring.

Status Epilepticus Dosing Regimen

Because of the increased risk of adverse cardiovascular reactions associated with rapid administration, do not administer fosphenytoin at a rate greater than 150 mg PE/min.

The dose of IV fosphenytoin (15 to 20 mg PE/kg) that is used to treat status epilepticus is administered at a maximum rate of 150 mg PE/min. The typical fosphenytoin infusion administered to a 50 kg patient would take between 5 and 7 minutes. Note that the delivery of an identical molar dose of phenytoin using parenteral phenytoin sodium or generic phenytoin sodium injection cannot be accomplished in less than 15 to 20 minutes because of the untoward cardiovascular effects that accompany the direct intravenous administration of phenytoin at rates greater than 50 mg/min.

If rapid phenytoin loading is a primary goal, IV administration of fosphenytoin is preferred because the time to achieve therapeutic plasma phenytoin concentrations is greater following IM than that following IV administration (see DOSAGE AND ADMINISTRATION).

Cardiovascular Risk Associated with Rapid Infusion

As non-emergency therapy, intravenous fosphenytoin should be administered more slowly. Because of the risks of cardiac and local toxicity associated with IV fosphenytoin, oral phenytoin should be used whenever possible.

Because adverse cardiovascular reactions have occurred during and after infusions, careful cardiac monitoring is needed during and after the administration of intravenous fosphenytoin. Reduction in rate of administration or discontinuation of dosing may be needed.

Adverse cardiovascular reactions include severe hypotension and cardiac arrhythmias. Cardiac arrhythmias have included bradycardia, heart block, QT interval prolongation, ventricular tachycardia, and ventricular fibrillation which have resulted in asystole, cardiac arrest, and death. Severe complications are most commonly encountered in critically ill patients, elderly patients, and patients with hypotension and severe myocardial insufficiency. However, cardiac events have also been reported in adults and children without underlying cardiac disease or comorbidities and at recommended doses and infusion rates.

Withdrawal Precipitated Seizure, Status Epilepticus

Antiepileptic drugs should not be abruptly discontinued because of the possibility of increased seizure frequency, including status epilepticus. When, in the judgment of the clinician, the need for dosage reduction, discontinuation, or substitution of alternative antiepileptic medication arises, this should be done gradually. However, in the event of an allergic or hypersensitivity reaction, rapid substitution of alternative therapy may be necessary. In this case, alternative therapy should be an antiepileptic drug not belonging to the hydantoin chemical class.

Serious Dermatologic Reactions

Serious and sometimes fatal dermatologic reactions, including toxic epidermal necrolysis (TEN) and Stevens-Johnson syndrome (SJS), have been reported with phenytoin treatment. The onset of symptoms is usually within 28 days, but can occur later. Fosphenytoin should be discontinued at the first sign of a rash, unless the rash is clearly not drug-related. If signs or symptoms suggest SJS/TEN, use of this drug should not be resumed and alternative therapy should be considered. If a rash occurs, the patient should be evaluated for signs and symptoms of Drug Reaction with Eosinophilia and Systemic Symptoms (see DRESS/Multiorgan Hypersensitivity below).

Studies in patients of Chinese ancestry have found a strong association between the risk of developing SJS/TEN and the presence of HLA-B*1502, an inherited allelic variant of the HLA B gene, in patients using carbamazepine. Limited evidence suggests that HLA-B*1502 may be a risk factor for the development of SJS/TEN in patients of Asian ancestry taking other antiepileptic drugs associated with SJS/TEN, including phenytoin. Consideration should be given to avoiding fosphenytoin as an alternative for carbamazepine patients positive for HLA-B*1502.

The use of HLA-B*1502 genotyping has important limitations and must never substitute for appropriate clinical vigilance and patient management. The role of other possible factors in the development of, and morbidity from, SJS/TEN, such as antiepileptic drug (AED) dose, compliance, concomitant medications, comorbidities, and the level of dermatologic monitoring have not been studied.

Drug Reaction with Eosinophilia and Systemic Symptoms (DRESS)/Multiorgan Hypersensitivity

Drug Reaction with Eosinophilia and Systemic Symptoms (DRESS), also known as Multiorgan hypersensitivity, has been reported in patients taking antiepileptic drugs, including phenytoin and fosphenytoin. Some of these events have been fatal or life-threatening. DRESS typically, although not exclusively, presents with fever, rash, and/or lymphadenopathy, in association with other organ system involvement, such as hepatitis, nephritis, hematological abnormalities, myocarditis, or myositis sometimes resembling an acute viral infection. Eosinophilia is often present. Because this disorder is variable in its expression, other organ systems not noted here may be involved. It is important to note that early manifestations of hypersensitivity, such as fever or lymphadenopathy, may be present even though rash is not evident. If such signs or symptoms are present, the patient should be evaluated immediately. Fosphenytoin should be discontinued if an alternative etiology for the signs or symptoms cannot be established.

Hypersensitivity

Fosphenytoin and other hydantoins are contraindicated in patients who have experienced phenytoin hypersensitivity (see CONTRAINDICATIONS). Additionally, consider alternatives to structurally similar drugs such as carboxamides (e.g., carbamazepine), barbiturates, succinimides, and oxazolidinediones (e.g., trimethadione) in these same patients. Similarly, if there is a history of hypersensitivity reactions to these structurally similar drugs in the patient or immediate family members, consider alternatives to fosphenytoin.

Hepatic Injury

Cases of acute hepatotoxicity, including infrequent cases of acute hepatic failure, have been reported with phenytoin. These events may be part of the spectrum of DRESS or may occur in isolation. Other common manifestations include jaundice, hepatomegaly, elevated serum transaminase levels, leukocytosis, and eosinophilia. The clinical course of acute phenytoin hepatotoxicity ranges from prompt recovery to fatal outcomes. In these patients with acute hepatotoxicity, fosphenytoin should be immediately discontinued and not readministered.

Hematopoietic System

Hematopoietic complications, some fatal, have occasionally been reported in association with administration of phenytoin. These have included thrombocytopenia, leukopenia, granulocytopenia, agranulocytosis, and pancytopenia with or without bone marrow suppression.

There have been a number of reports that have suggested a relationship between phenytoin and the development of lymphadenopathy (local or generalized), including benign lymph node hyperplasia, pseudolymphoma, lymphoma, and Hodgkin’s disease. Although a cause and effect relationship has not been established, the occurrence of lymphadenopathy indicates the need to differentiate such a condition from other types of lymph node pathology. Lymph node involvement may occur with or without symptoms and signs resembling DRESS. In all cases of lymphadenopathy, follow-up observation for an extended period is indicated and every effort should be made to achieve seizure control using alternative antiepileptic drugs.

Alcohol Use

Acute alcohol intake may increase plasma phenytoin concentrations while chronic alcohol use may decrease plasma concentrations.

Usage in Pregnancy

Clinical

Risks to Mother

An increase in seizure frequency may occur during pregnancy because of altered phenytoin pharmacokinetics. Periodic measurement of plasma phenytoin concentrations may be valuable in the management of pregnant women as a guide to appropriate adjustment of dosage (see PRECAUTIONS, Laboratory Tests). However, postpartum restoration of the original dosage will probably be indicated.

Risks to the Fetus

If this drug is used during pregnancy, or if the patient becomes pregnant while taking the drug, the patient should be apprised of the potential harm to the fetus.

Prenatal exposure to phenytoin may increase the risks for congenital malformations and other adverse developmental outcomes. Increased frequencies of major malformations (such as orofacial clefts and cardiac defects), minor anomalies (dysmorphic facial features, nail and digit hypoplasia), growth abnormalities (including microcephaly), and mental deficiency have been reported among children born to epileptic women who took phenytoin alone or in combination with other antiepileptic drugs during pregnancy. There have also been several reported cases of malignancies, including neuroblastoma, in children whose mothers received phenytoin during pregnancy. The overall incidence of malformations for children of epileptic women treated with antiepileptic drugs (phenytoin and/or others) during pregnancy is about 10%, or two-to three-fold that in the general population. However, the relative contributions of antiepileptic drugs and other factors associated with epilepsy to this increased risk are uncertain and in most cases it has not been possible to attribute specific developmental abnormalities to particular antiepileptic drugs. Patients should consult with their physicians to weigh the risks and benefits of phenytoin during pregnancy.

Postpartum Period

A potentially life-threatening bleeding disorder related to decreased levels of vitamin K-dependent clotting factors may occur in newborns exposed to phenytoin in utero. This drug-induced condition can be prevented with vitamin K administration to the mother before delivery and to the neonate after birth.

Nonclinical

Administration of phenytoin to pregnant animals resulted in teratogenicity (increased incidences of fetal malformations) and other developmental toxicity (including embryofetal death, growth impairment, and behavioral abnormalities) in multiple animal species at clinically relevant doses.

PRECAUTIONS

General: (Fosphenytoin specific)

Sensory Disturbances

Severe burning, itching, and/or paresthesia were reported by 7 of 16 normal volunteers administered IV fosphenytoin at a dose of 1200 mg PE at the maximum rate of administration (150 mg PE/min). The severe sensory disturbance lasted from 3 to 50 minutes in 6 of these subjects and for 14 hours in the seventh subject. In some cases, milder sensory disturbances persisted for as long as 24 hours. The location of the discomfort varied among subjects with the groin mentioned most frequently as an area of discomfort. In a separate cohort of 16 normal volunteers (taken from 2 other studies) who were administered IV fosphenytoin at a dose of 1200 mg PE at the maximum rate of administration (150 mg PE/min), none experienced severe disturbances, but most experienced mild to moderate itching or tingling.

Patients administered fosphenytoin at doses of 20 mg PE/kg at 150 mg PE/min are expected to experience discomfort of some degree. The occurrence and intensity of the discomfort can be lessened by slowing or temporarily stopping the infusion.

The effect of continuing infusion unaltered in the presence of these sensations is unknown. No permanent sequelae have been reported thus far. The pharmacologic basis for these positive sensory phenomena is unknown, but other phosphate ester drugs, which deliver smaller phosphate loads, have been associated with burning, itching, and/or tingling predominantly in the groin area.

Local Toxicity (Purple Glove Syndrome)

Edema, discoloration, and pain distal to the site of injection (described as “purple glove syndrome”) have also been reported following peripheral intravenous fosphenytoin injection. This may or may not be associated with extravasation. The syndrome may not develop for several days after injection.

Phosphate Load

The phosphate load provided by fosphenytoin (0.0037 mmol phosphate/mg PE fosphenytoin) should be considered when treating patients who require phosphate restriction, such as those with severe renal impairment.

IV Loading in Renal and/or Hepatic Disease or in Those with Hypoalbuminemia

After IV administration to patients with renal and/or hepatic disease, or in those with hypoalbuminemia, fosphenytoin clearance to phenytoin may be increased without a similar increase in phenytoin clearance. This has the potential to increase the frequency and severity of adverse events (see CLINICAL PHARMACOLOGY, Special Populations and DOSAGE AND ADMINISTRATION, Dosing in Special Populations).

General: (phenytoin associated)

Fosphenytoin is not indicated for the treatment of absence seizures.

A small percentage of individuals who have been treated with phenytoin have been shown to metabolize the drug slowly. Slow metabolism may be due to limited enzyme availability and lack of induction; it appears to be genetically determined.

Phenytoin has been infrequently associated with the exacerbation of porphyria. Caution should be exercised when fosphenytoin is used in patients with this disease.

Hyperglycemia, resulting from phenytoin’s inhibitory effect on insulin release, has been reported. Phenytoin may also raise the serum glucose concentrations in diabetic patients.

Plasma concentrations of phenytoin sustained above the optimal range may produce confusional states referred to as “delirium,” “psychosis,” or “encephalopathy,” or rarely, irreversible cerebellar dysfunction. Accordingly, at the first sign of acute toxicity, determination of plasma phenytoin concentrations is recommended (see PRECAUTIONS, Laboratory Tests). Fosphenytoin dose reduction is indicated if phenytoin concentrations are excessive; if symptoms persist, administration of fosphenytoin should be discontinued.

The liver is the primary site of biotransformation of phenytoin; patients with impaired liver function, elderly patients, or those who are gravely ill may show early signs of toxicity.

Phenytoin and other hydantoins are not indicated for seizures due to hypoglycemic or other metabolic causes. Appropriate diagnostic procedures should be performed as indicated.

Phenytoin has the potential to lower serum folate levels.

Laboratory Tests

Phenytoin doses are usually selected to attain therapeutic plasma total phenytoin concentrations of 10 to 20 mcg/mL, (unbound phenytoin concentrations of 1 to 2 mcg/mL). Following fosphenytoin administration, it is recommended that phenytoin concentrations not be monitored until conversion to phenytoin is essentially complete. This occurs within approximately 2 hours after the end of IV infusion and 4 hours after IM injection.

Prior to complete conversion, commonly used immunoanalytical techniques, such as TDx®/TDxFLxTM (fluorescence polarization) and Emit® 2000 (enzyme multiplied), may significantly overestimate plasma phenytoin concentrations because of cross-reactivity with fosphenytoin. The error is dependent on plasma phenytoin and fosphenytoin concentration (influenced by fosphenytoin dose, route and rate of administration, and time of sampling relative to dosing), and analytical method. Chromatographic assay methods accurately quantitate phenytoin concentrations in biological fluids in the presence of fosphenytoin. Prior to complete conversion, blood samples for phenytoin monitoring should be collected in tubes containing EDTA as an anticoagulant to minimize ex vivo conversion of fosphenytoin to phenytoin. However, even with specific assay methods, phenytoin concentrations measured before conversion of fosphenytoin is complete will not reflect phenytoin concentrations ultimately achieved.

Drug Interactions

No drugs are known to interfere with the conversion of fosphenytoin to phenytoin. Conversion could be affected by alterations in the level of phosphatase activity, but given the abundance and wide distribution of phosphatases in the body it is unlikely that drugs would affect this activity enough to affect conversion of fosphenytoin to phenytoin. Drugs highly bound to albumin could increase the unbound fraction of fosphenytoin. Although, it is unknown whether this could result in clinically significant effects, caution is advised when administering fosphenytoin with other drugs that significantly bind to serum albumin.

The pharmacokinetics and protein binding of fosphenytoin, phenytoin, and diazepam were not altered when diazepam and fosphenytoin were concurrently administered in single submaximal doses.

The most significant drug interactions following administration of fosphenytoin are expected to occur with drugs that interact with phenytoin. Phenytoin is extensively bound to serum plasma proteins and is prone to competitive displacement. Phenytoin is metabolized by hepatic cytochrome P450 enzymes CYP2C9 and CYP2C19 and is particularly susceptible to inhibitory drug interactions because it is subject to saturable metabolism. Inhibition of metabolism may produce significant increases in circulating phenytoin concentrations and enhance the risk of drug toxicity. Phenytoin is a potent inducer of hepatic drug-metabolizing enzymes.

The most commonly occurring drug interactions are listed below:

Note: The list is not intended to be inclusive or comprehensive. Individual drug package inserts should be consulted.

Drugs that affect phenytoin concentrations:

- Drugs that may increase plasma phenytoin concentrations include: acute alcohol intake, amiodarone, anti-epileptic agents (ethosuximide, felbamate, oxcarbazepine, methsuximide, topiramate), azoles (fluconazole, ketoconazole, itraconazole, miconazole, voriconazole), capecitabine, chloramphenicol, chlordiazepoxide, disulfiram, estrogens, fluorouracil, fluoxetine, fluvastatin, fluvoxamine, H2-antagonists (e.g. cimetidine), halothane, isoniazid, methylphenidate, omeprazole, phenothiazines, salicylates, sertraline, succinimides, sulfonamides (e.g., sulfamethizole, sulfaphenazole, sulfadiazine, sulfamethoxazole-trimethoprim), tacrolimus, ticlopidine, tolbutamide, trazodone and warfarin.
- Drugs that may decrease plasma phenytoin concentrations include: anticancer drugs usually in combination (e.g., bleomycin, carboplatin, cisplatin, doxorubicin, methotrexate), carbamazepine, chronic alcohol abuse, diazepam, diazoxide, folic acid, fosamprenavir, nelfinavir, reserpine, rifampin, ritonavir, St. John’s Wort, theophylline and vigabatrin.
- Drugs that may either increase or decrease plasma phenytoin concentrations include: phenobarbital, valproic acid and sodium valproate. Similarly, the effects of phenytoin on phenobarbital, valproic acid and sodium plasma valproate concentrations are unpredictable.
- The addition or withdrawal of these agents in patients on phenytoin therapy may require an adjustment of the phenytoin dose to achieve optimal clinical outcome.

Drugs affected by phenytoin:

- Drugs that should not be coadministered with phenytoin: Delavirdine (see CONTRAINDICATIONS).
- Drugs whose efficacy is impaired by phenytoin include: azoles (fluconazole, ketoconazole, itraconazole, voriconazole, posaconazole), corticosteroids, doxycycline, estrogens, furosemide, irinotecan, oral contraceptives, paclitaxel, paroxetine, quinidine, rifampin, sertraline, teniposide, theophylline and vitamin D.
- Increased and decreased PT/INR responses have been reported when phenytoin is coadministered with warfarin.
- Phenytoin decreases plasma concentrations of active metabolites of albendazole, certain HIV antivirals (efavirenz, lopinavir/ritonavir, indinavir, nelfinavir, ritonavir, saquinavir), anti-epileptic agents (carbamazepine, felbamate, lamotrigine, topiramate, oxcarbazepine, quetiapine), atorvastatin, chlorpropamide, clozapine, cyclosporine, digoxin, fluvastatin, folic acid, methadone, mexiletine, nifedipine, nimodipine, nisoldipine, praziquantel, simvastatin and verapamil.
- Phenytoin when given with fosamprenavir alone may decrease the concentration of amprenavir, the active metabolite. Phenytoin when given with the combination of fosamprenavir and ritonavir may increase the concentration of amprenavir.
- Resistance to the neuromuscular blocking action of the nondepolarizing neuromuscular blocking agents pancuronium, vecuronium, rocuronium and cisatracurium has occurred in patients chronically administered phenytoin. Whether or not phenytoin has the same effect on other non-depolarizing agents is unknown. Patients should be monitored closely for more rapid recovery from neuromuscular blockade than expected, and infusion rate requirements may be higher.
- The addition or withdrawal of phenytoin during concomitant therapy with these agents may require adjustment of the dose of these agents to achieve optimal clinical outcome.

Monitoring of plasma phenytoin concentrations may be helpful when possible drug interactions are suspected (see Laboratory Tests).

Drug/Laboratory Test Interactions

Phenytoin may decrease serum concentrations of T4. It may also produce artifactually low results in dexamethasone or metyrapone tests. Phenytoin may also cause increased serum concentrations of glucose, alkaline phosphatase, and gamma glutamyl transpeptidase (GGT). Care should be taken when using immunoanalytical methods to measure plasma concentrations following fosphenytoin administration (see Laboratory Tests).

Carcinogenesis, Mutagenesis, Impairment of Fertility

Carcinogenesis: See WARNINGS (Hematopoietic System) section

The carcinogenic potential of fosphenytoin has not been assessed. In 2-year carcinogenicity studies, phenytoin (active metabolite of fosphenytoin) was administered in the diet at doses of 0, 10, 25, or 45 mg/kg/day (mice) and 0, 25, 50, or 100 mg/kg/day (rats). In mice, hepatocellular tumors were increased in males and females at the highest dose tested. No drug-related increase in tumors was observed in rats. The peak phenytoin levels at the highest doses tested were lower than those in humans at therapeutic concentrations.

In published 2-year carcinogenicity studies, phenytoin was administered in the diet at up to 600 ppm (approximately 90 mg/kg/day) to mice and up to 2400 ppm (approximately 120 mg/kg/day) to rats. The incidence of hepatocellular tumors was increased in mice. No drug-related increase in tumors was observed in rats.

Mutagenesis

An increase in structural chromosome aberrations were observed in cultured V79 Chinese hamster lung cells exposed to fosphenytoin in the presence of metabolic activation. No evidence of mutagenicity was observed in bacteria (Ames test) or Chinese hamster lung cells in vitro, and no evidence for clastogenic activity was observed in an in vivo mouse bone marrow micronucleus assay.

Fertility

Fosphenytoin was administered to male and female rats during mating and continuing in females throughout gestation and lactation at doses of 50 mg PE/kg or higher. No effects on fertility were observed in males. In females, altered estrous cycles, delayed mating, prolonged gestation length, and developmental toxicity were observed at all doses, which were associated with maternal toxicity. The lowest dose tested is approximately 40% of the maximum human loading dose on a mg/m^2 basis.

Pregnancy - Category D:

(see WARNINGS)

Use in Nursing Mothers

It is not known whether fosphenytoin is excreted in human milk.

Following administration of phenytoin sodium, phenytoin appears to be excreted in low concentrations in human milk. Therefore, breast-feeding is not recommended for women receiving fosphenytoin.

Pediatric Use

Safety and effectiveness of fosphenytoin in pediatric patients has not been established.

Geriatric Use

No systematic studies in geriatric patients have been conducted. Phenytoin clearance tends to decrease with increasing age (see CLINICAL PHARMACOLOGY, Special Populations).

ADVERSE REACTIONS

The more important adverse clinical events caused by the IV use of fosphenytoin or phenytoin are cardiovascular collapse and/or central nervous system depression. Hypotension can occur when either drug is administered rapidly by the IV route. The rate of administration is very important; for fosphenytoin, it should not exceed 150 mg PE/min.

The adverse clinical events most commonly observed with the use of fosphenytoin in clinical trials were nystagmus, dizziness, pruritus, paresthesia, headache, somnolence, and ataxia. With two exceptions, these events are commonly associated with the administration of IV phenytoin. Paresthesia and pruritus, however, were seen much more often following fosphenytoin administration and occurred more often with IV fosphenytoin administration than with IM fosphenytoin administration. These events were dose and rate related; most alert patients (41 of 64; 64%) administered doses of ≥15 mg PE/kg at 150 mg PE/min experienced discomfort of some degree. These sensations, generally described as itching, burning, or tingling, were usually not at the infusion site. The location of the discomfort varied with the groin mentioned most frequently as a site of involvement. The paresthesia and pruritus were transient events that occurred within several minutes of the start of infusion and generally resolved within 10 minutes after completion of fosphenytoin infusion. Some patients experienced symptoms for hours. These events did not increase in severity with repeated administration. Concurrent adverse events or clinical laboratory change suggesting an allergic process were not seen (see PRECAUTIONS, Sensory Disturbances).

Approximately 2% of the 859 individuals who received fosphenytoin in premarketing clinical trials discontinued treatment because of an adverse event. The adverse events most commonly associated with withdrawal were pruritus (0.5%), hypotension (0.3%), and bradycardia (0.2%).

Dose and Rate Dependency of Adverse Events Following IV Fosphenytoin:

The incidence of adverse events tended to increase as both dose and infusion rate increased. In particular, at doses of ≥15 mg PE/kg and rates ≥150 mg PE/min, transient pruritus, tinnitus, nystagmus, somnolence, and ataxia occurred 2 to 3 times more often than at lower doses or rates.

Incidence in Controlled Clinical Trials

All adverse events were recorded during the trials by the clinical investigators using terminology of their own choosing. Similar types of events were grouped into standardized categories using modified COSTART dictionary terminology. These categories are used in the tables and listings below with the frequencies representing the proportion of individuals exposed to fosphenytoin or comparative therapy.

The prescriber should be aware that these figures cannot be used to predict the frequency of adverse events in the course of usual medical practice where patient characteristics and other factors may differ from those prevailing during clinical studies. Similarly, the cited frequencies cannot be directly compared with figures obtained from other clinical investigations involving different treatments, uses or investigators. An inspection of these frequencies, however, does provide the prescribing physician with one basis to estimate the relative contribution of drug and nondrug factors to the adverse event incidences in the population studied.

Incidence in Controlled Clinical Trials - IV Administration To Patients With Epilepsy or Neurosurgical Patients: Table 2 lists treatment-emergent adverse events that occurred in at least 2% of patients treated with IV fosphenytoin at the maximum dose and rate in a randomized, double-blind, controlled clinical trial where the rates for phenytoin and fosphenytoin administration would have resulted in equivalent systemic exposure to phenytoin.

TABLE 2. Treatment-Emergent Adverse Event Incidence Following IV Administration at the Maximum Dose and Rate to Patients with Epilepsy or Neurosurgical Patients (Events in at Least 2% of Fosphenytoin-Treated Patients)
BODY SYSTEM Adverse Event | IV Fosphenytoin N=90 | IV Phenytoin N=22
BODY AS A WHOLE
Pelvic Pain | 4.4 | 0
Asthenia | 2.2 | 0
Back Pain | 2.2 | 0
Headache | 2.2 | 4.5
CARDIOVASCULAR
Hypotension | 7.7 | 9.1
Vasodilatation | 5.6 | 4.5
Tachycardia | 2.2 | 0
DIGESTIVE
Nausea | 8.9 | 13.6
Tongue Disorder | 4.4 | 0
Dry Mouth | 4.4 | 4.5
Vomiting | 2.2 | 9.1
NERVOUS
Nystagmus | 44.4 | 59.1
Dizziness | 31.1 | 27.3
Somnolence | 20 | 27.3
Ataxia | 11.1 | 18.2
Stupor | 7.7 | 4.5
Incoordination | 4.4 | 4.5
Paresthesia | 4.4 | 0
Extrapyramidal Syndrome | 4.4 | 0
Tremor | 3.3 | 9.1
Agitation | 3.3 | 0
Hypesthesia | 2.2 | 9.1
Dysarthria | 2.2 | 0
Vertigo | 2.2 | 0
Brain Edema | 2.2 | 4.5
SKIN AND APPENDAGES
Pruritus | 48.9 | 4.5
SPECIAL SENSES
Tinnitus | 8.9 | 9.1
Diplopia | 3.3 | 0
Taste Perversion | 3.3 | 0
Amblyopia | 2.2 | 9.1
Deafness | 2.2 | 0

Incidence in Controlled Trials - IM Administration To Patients With Epilepsy: Table 3 lists treatment-emergent adverse events that occurred in at least 2% of fosphenytoin-treated patients in a double-blind, randomized, controlled clinical trial of adult epilepsy patients receiving either IM fosphenytoin substituted for oral phenytoin sodium or continuing oral phenytoin sodium. Both treatments were administered for 5 days.

TABLE 3. Treatment-Emergent Adverse Event Incidence Following Substitution of IM Fosphenytoin for Oral Phenytoin Sodium in Patients With Epilepsy (Events in at Least 2% of Fosphenytoin-Treated Patients)
BODY SYSTEM Adverse Event | IM Fosphenytoin N=179 | Oral Phenytoin Sodium N=61
BODY AS A WHOLE
Headache | 8.9 | 4.9
Asthenia | 3.9 | 3.3
Accidental Injury | 3.4 | 6.6
DIGESTIVE
Nausea | 4.5 | 0
Vomiting | 2.8 | 0
HEMATOLOGIC AND LYMPHATIC
Ecchymosis | 7.3 | 4.9
NERVOUS
Nystagmus | 15.1 | 8.2
Tremor | 9.5 | 13.1
Ataxia | 8.4 | 8.2
Incoordination | 7.8 | 4.9
Somnolence | 6.7 | 9.8
Dizziness | 5 | 3.3
Paresthesia | 3.9 | 3.3
Reflexes Decreased | 2.8 | 4.9
SKIN AND APPENDAGES
Pruritus | 2.8 | 0

Adverse Events During All Clinical Trials

Fosphenytoin has been administered to 859 individuals during all clinical trials. All adverse events seen at least twice are listed in the following, except those already included in previous tables and listings. Events are further classified within body system categories and enumerated in order of decreasing frequency using the following definitions: frequent adverse events are defined as those occurring in greater than 1/100 individuals; infrequent adverse events are those occurring in 1/100 to 1/1000 individuals.

Body as a Whole: Frequent: fever, injection-site reaction, infection, chills, face edema, injection-site pain; Infrequent: sepsis, injection-site inflammation, injection-site edema, injection-site hemorrhage, flu syndrome, malaise, generalized edema, shock, photosensitivity reaction, cachexia, cryptococcosis.

Cardiovascular: Frequent: hypertension; Infrequent: cardiac arrest, migraine, syncope, cerebral hemorrhage, palpitation, sinus bradycardia, atrial flutter, bundle branch block, cardiomegaly, cerebral infarct, postural hypotension, pulmonary embolus, QT interval prolongation, thrombophlebitis, ventricular extrasystoles, congestive heart failure.

Digestive: Frequent: constipation; Infrequent: dyspepsia, diarrhea, anorexia, gastrointestinal hemorrhage, increased salivation, liver function tests abnormal, tenesmus, tongue edema, dysphagia, flatulence, gastritis, ileus.

Endocrine: Infrequent: diabetes insipidus.

Hematologic and Lymphatic: Infrequent: thrombocytopenia, anemia, leukocytosis, cyanosis,

hypochromic anemia, leukopenia, lymphadenopathy, petechia.

Metabolic and Nutritional: Frequent: hypokalemia; Infrequent: hyperglycemia, hypophosphatemia, alkalosis, acidosis, dehydration, hyperkalemia, ketosis.

Musculoskeletal: Frequent: myasthenia; Infrequent: myopathy, leg cramps, arthralgia, myalgia.

Nervous: Frequent: reflexes increased, speech disorder, dysarthria, intracranial hypertension, thinking abnormal, nervousness, hypesthesia; Infrequent: confusion, twitching, Babinski sign positive, circumoral paresthesia, hemiplegia, hypotonia, convulsion, extrapyramidal syndrome, insomnia, meningitis, depersonalization, CNS depression, depression, hypokinesia, hyperkinesia, brain edema, paralysis, psychosis, aphasia, emotional lability, coma, hyperesthesia, myoclonus, personality disorder, acute brain syndrome, encephalitis, subdural hematoma, encephalopathy, hostility, akathisia, amnesia, neurosis.

Respiratory: Frequent: pneumonia; Infrequent: pharyngitis, sinusitis, hyperventilation, rhinitis, apnea, aspiration pneumonia, asthma, dyspnea, atelectasis, cough increased, sputum increased, epistaxis, hypoxia, pneumothorax, hemoptysis, bronchitis.

Skin and Appendages: Frequent: rash; Infrequent: maculopapular rash, urticaria, sweating, skin discoloration, contact dermatitis, pustular rash, skin nodule.

Special Senses: Frequent: taste perversion; Infrequent: deafness, visual field defect, eye pain, conjunctivitis, photophobia, hyperacusis, mydriasis, parosmia, ear pain, taste loss.

Urogenital: Infrequent: urinary retention, oliguria, dysuria, vaginitis, albuminuria, genital edema, kidney failure, polyuria, urethral pain, urinary incontinence, vaginal moniliasis.

Post-Marketing Experience

The following adverse reactions have been identified during postapproval use of fosphenytoin. Because these reactions are reported voluntarily from a population of uncertain size, it is not always possible to reliably estimate their frequency or establish a causal relationship to drug exposure.

There have been post-marketing reports of anaphylactoid reaction and anaphylaxis.

Other Phenytoin-Associated Adverse Events:

Dyskinesia.

OVERDOSAGE

Nausea, vomiting, lethargy, tachycardia, bradycardia, asystole, cardiac arrest, hypotension, syncope, hypocalcemia, metabolic acidosis, and death have been reported in cases of overdosage with fosphenytoin.

The median lethal dose of fosphenytoin given intravenously in mice and rats was 156 mg PE/kg and approximately 250 mg PE/kg, or about 0.6 and 2 times, respectively, the maximum human loading dose on a mg/m^2 basis. Signs of acute toxicity in animals included ataxia, labored breathing, ptosis, and hypoactivity.

Because fosphenytoin is a prodrug of phenytoin, the following information may be helpful. Initial symptoms of acute phenytoin toxicity are nystagmus, ataxia, and dysarthria. Other signs include tremor, hyperreflexia, lethargy, slurred speech, nausea, vomiting, coma, and hypotension. Depression of respiratory and circulatory systems leads to death. There are marked variations among individuals with respect to plasma phenytoin concentrations where toxicity occurs. Lateral gaze nystagmus usually appears at 20 mcg/mL, ataxia at 30 mcg/mL, and dysarthria and lethargy appear when the plasma concentration is over 40 mcg/mL. However, phenytoin concentrations as high as 50 mcg/mL have been reported without evidence of toxicity. As much as 25 times the therapeutic phenytoin dose has been taken, resulting in plasma phenytoin concentrations over 100 mcg/mL, with complete recovery.

Treatment is nonspecific since there is no known antidote to fosphenytoin or phenytoin overdosage. The adequacy of the respiratory and circulatory systems should be carefully observed, and appropriate supportive measures employed. Hemodialysis can be considered since phenytoin is not completely bound to plasma proteins. Total exchange transfusion has been used in the treatment of severe intoxication in children. In acute overdosage the possibility of other CNS depressants, including alcohol, should be borne in mind.

Formate and phosphate are metabolites of fosphenytoin and therefore may contribute to signs of toxicity following overdosage. Signs of formate toxicity are similar to those of methanol toxicity and are associated with severe anion-gap metabolic acidosis. Large amounts of phosphate, delivered rapidly, could potentially cause hypocalcemia with paresthesia, muscle spasms, and seizures. Ionized free calcium levels can be measured and, if low, used to guide treatment.

DOSAGE AND ADMINISTRATION

The dose, concentration, and infusion rate of intravenous fosphenytoin should always be expressed as phenytoin sodium equivalents (PE). There is no need to perform molecular weight-based adjustments when converting between fosphenytoin and phenytoin sodium doses. Fosphenytoin should always be prescribed and dispensed in phenytoin sodium equivalent units (PE). 1.5 mg of fosphenytoin sodium is equivalent to 1 mg phenytoin sodium, and is referred to as 1 mg PE. The amount and concentration of fosphenytoin is always expressed in terms of mg of phenytoin sodium equivalents (mg PE).

Do not confuse the concentration of fosphenytoin with the total amount of drug in the vial.

Caution must be used when administering fosphenytoin due to the risk of dosing errors (see WARNINGS). Medication errors associated with fosphenytoin have resulted in patients receiving the wrong dose of fosphenytoin. Fosphenytoin is marketed in 2 mL vials containing a total of 100 mg PE and 10 mL vials containing a total of 500 mg PE. Both vials contain a concentration of 50 mg PE/mL. Errors have occurred when the concentration of the vial (50 mg PE/mL) was misinterpreted to mean that the total content of the vial was 50 mg PE. These errors have resulted in two- or ten-fold overdoses of fosphenytoin since each of the vials actually contains a total of 100 mg PE or 500 mg PE. In some cases, ten-fold overdoses were associated with fatal outcomes. To help minimize confusion, the prescribed dose of fosphenytoin should always be expressed in milligrams of phenytoin equivalents (mg PE). Additionally, when ordering and storing fosphenytoin, consider displaying the total drug content (i.e., 100 mg PE/ 2 mL or 500 mg PE/ 10 mL) instead of concentration in computer systems, pre-printed orders, and automated dispensing cabinet databases to help ensure that total drug content can be clearly identified. Care should be taken to ensure the appropriate volume of fosphenytoin is withdrawn from the vial when preparing the dose for administration. Attention to these details may prevent some fosphenytoin medication errors from occurring.

Prior to intravenous infusion, dilute fosphenytoin injection in 5% dextrose or 0.9% saline solution for injection to a concentration ranging from 1.5 to 25 mg PE/mL. The maximum concentration of fosphenytoin in any solution should be 25 mg PE/mL. When fosphenytoin is given as an intravenous infusion, fosphenytoin needs to be diluted and should only be administered at a rate not exceeding 150 mg PE/min.

Parenteral drug products should be inspected visually for particulate matter or discoloration prior to administration, whenever solution and container permit.

Status Epilepticus

- The loading dose of fosphenytoin is 15 to 20 mg PE/kg administered at 100 to 150 mg PE/min.
- Because of the risk of hypotension, fosphenytoin should be administered no faster than 150 mg PE/min. Continuous monitoring of the electrocardiogram, blood pressure, and respiratory function is essential and the patient should be observed throughout the period where maximal serum phenytoin concentrations occur, approximately 10 to 20 minutes after the end of fosphenytoin infusions.
- Because the full antiepileptic effect of phenytoin, whether given as fosphenytoin or parenteral phenytoin, is not immediate, other measures, including concomitant administration of an intravenous benzodiazepine, will usually be necessary for the control of status epilepticus.
- The loading dose should be followed by maintenance doses of either fosphenytoin or phenytoin.

If administration of fosphenytoin does not terminate seizures, the use of other anticonvulsants and other appropriate measures should be considered.

Even though loading doses of fosphenytoin have been given by the intramuscular route for other indications when intravenous access is impossible, intramuscular fosphenytoin should ordinarily not be used in the treatment of status epilepticus because therapeutic phenytoin concentrations may not be reached as quickly as with intravenous administration.

Nonemergent Loading and Maintenance Dosing

Because of the risks of cardiac and local toxicity associated with intravenous fosphenytoin, oral phenytoin should be used whenever possible.

The loading dose of fosphenytoin is 10 to 20 mg PE/kg given intravenous or intramuscular. The rate of administration for intravenous fosphenytoin should be no greater than 150 mg PE/min. Continuous monitoring of the electrocardiogram, blood pressure, and respiratory function is essential and the patient should be observed throughout the period where maximal serum phenytoin concentrations occur (approximately 20 minutes after the end of fosphenytoin infusion).

The initial daily maintenance dose of fosphenytoin is 4 to 6 mg PE/kg/day in divided doses.

Intramuscular or Intravenous Substitution for Oral Phenytoin Therapy

When treatment with oral phenytoin is not possible, fosphenytoin can be substituted for oral phenytoin at the same total daily dose.

Phenytoin sodium capsules are approximately 90% bioavailable by the oral route. Phenytoin, supplied as fosphenytoin, is 100% bioavailable by both the intramuscular and intravenous routes. For this reason, plasma phenytoin concentrations may increase modestly when intramuscular or intravenous fosphenytoin is substituted for oral phenytoin sodium therapy.

The rate of administration for intravenous fosphenytoin should be no greater than 150 mg PE/min.

In controlled trials, intramuscular fosphenytoin was administered as a single daily dose utilizing either 1 or 2 injection sites. Some patients may require more frequent dosing.

Dosing in Special Populations

Patients with Renal or Hepatic Disease: Due to an increased fraction of unbound phenytoin in patients with renal or hepatic disease, or in those with hypoalbuminemia, the interpretation of total phenytoin plasma concentrations should be made with caution (see CLINICAL PHARMACOLOGY, Special Populations). Unbound phenytoin concentrations may be more useful in these patient populations. After intravenous fosphenytoin administration to patients with renal and/or hepatic disease, or in those with hypoalbuminemia, fosphenytoin clearance to phenytoin may be increased without a similar increase in phenytoin clearance. This has the potential to increase the frequency and severity of adverse events (see PRECAUTIONS).

Elderly Patients: Age does not have a significant impact on the pharmacokinetics of fosphenytoin following fosphenytoin administration. Phenytoin clearance is decreased slightly in elderly patients and lower or less frequent dosing may be required.

Pediatric: The safety and efficacy of fosphenytoin in pediatric patients have not been established.

HOW SUPPLIED

Fosphenytoin Sodium Injection, USP is supplied as follows:

10 mL per vial [NDC 65162-999-01] — Each 10 mL vial contains Fosphenytoin Sodium, USP 750 mg equivalent to 500 mg of phenytoin sodium, USP: (Packages of 10 - NDC 65162-999-10).

2 mL per vial [NDC 65162-998-01] — Each 2 mL vial contains Fosphenytoin Sodium, USP 150 mg equivalent to 100 mg of phenytoin sodium, USP: (Packages of 25 - NDC 65162-998-25).

Both sizes of vials contain Tromethamine, USP (TRIS), Hydrochloric Acid, NF, or Sodium Hydroxide, NF, and Water for Injection, USP.

Fosphenytoin sodium should always be prescribed in phenytoin sodium equivalents (PE) (see DOSAGE AND ADMINISTRATION).

1.5 mg of fosphenytoin sodium is equivalent to 1 mg phenytoin sodium, and is referred to as 1 mg PE. The amount and concentration of fosphenytoin is always expressed in terms of mg of phenytoin sodium equivalents (PE). Fosphenytoin’s weight is expressed as phenytoin sodium equivalents to avoid the need to perform molecular weight-based adjustments when substituting fosphenytoin for phenytoin or vice versa.

Store under refrigeration at 2°C to 8°C (36°F to 46°F). The product should not be stored at room temperature for more than 48 hours. Vials that develop particulate matter should not be used.

Brands listed are the trademarks of their respective owners.

Made in India

Distributed by:
Amneal Pharmaceuticals
Bridgewater, NJ 08807

Rev. 10-2015-03

PACKAGE LABEL.PRINCIPAL DISPLAY PANEL

100 mg Label

PACKAGE LABEL.PRINCIPAL DISPLAY PANEL

100 mg Carton

PACKAGE LABEL.PRINCIPAL DISPLAY PANEL

500 mg Label

PACKAGE LABEL.PRINCIPAL DISPLAY PANEL

500 mg Carton